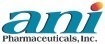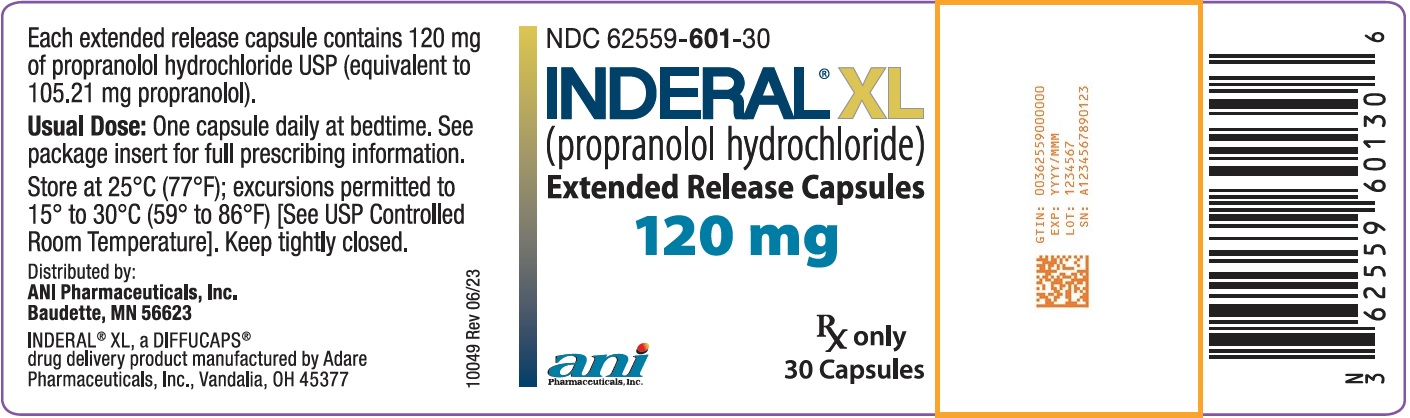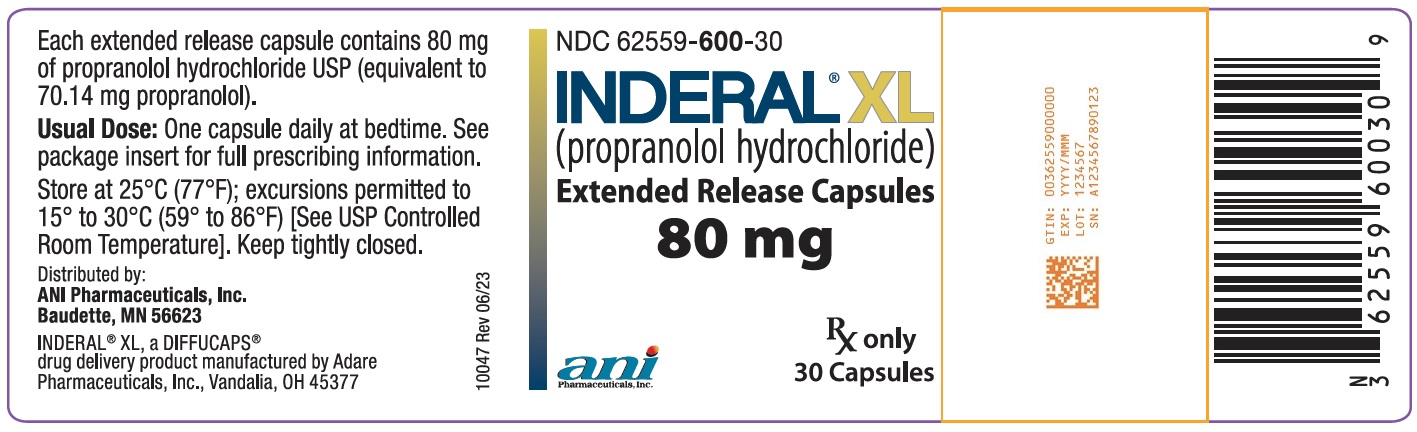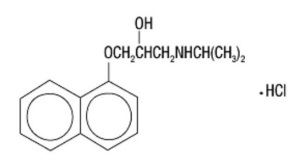 DRUG LABEL: Inderal XL
NDC: 62559-600 | Form: CAPSULE, EXTENDED RELEASE
Manufacturer: ANI Pharmaceuticals, Inc.
Category: prescription | Type: HUMAN PRESCRIPTION DRUG LABEL
Date: 20240320

ACTIVE INGREDIENTS: PROPRANOLOL HYDROCHLORIDE 80 mg/1 1
INACTIVE INGREDIENTS: SUCROSE; STARCH, CORN; ETHYLCELLULOSE (10 MPA.S); POVIDONE K30; HYPROMELLOSE PHTHALATE (31% PHTHALATE, 40 CST); DIETHYL PHTHALATE; HYPROMELLOSE 2910 (6 MPA.S); POLYETHYLENE GLYCOL 400; POLYETHYLENE GLYCOL 8000; GELATIN, UNSPECIFIED; TITANIUM DIOXIDE; FD&C BLUE NO. 2

HIGHLIGHTS OF PRESCRIBING INFORMATION

These highlights do not include all the information needed to use INDERAL XL safely and effectively. See full prescribing information for INDERAL XL.
INDERAL XL (propranolol hydrochloride) extended release capsules, for oral use
Initial U.S. Approval: 2003

RECENT MAJOR CHANGES

Warnings and Precautions, Hypoglycemia (5.4) 5/2023

1 INDICATIONS AND USAGE

INDERAL XL is a beta adrenergic blocker indicated for the treatment of hypertension, to lower blood pressure. Lowering blood pressure reduces the risk of fatal and nonfatal cardiovascular events, primarily strokes and myocardial infarctions. (1)

2 DOSAGE AND ADMINISTRATION

- Administer once daily at bedtime consistently either on an empty stomach or with food. (2)
- Initiate dosage at 80 mg and titrate up to 120 mg if needed. (2)

3 DOSAGE FORMS AND STRENGTHS

Capsules: 80 mg, 120 mg. (3)

4 CONTRAINDICATIONS

- Cardiogenic shock and decompensated heart failure. (4)
- Sinus bradycardia, sick sinus syndrome, and greater than first-degree block unless a permanent pacemaker is in place. (4)
- Bronchial asthma. (4)
- Hypersensitivity to propranolol or any of the components of INDERAL XL. (4)

5 WARNINGS AND PRECAUTIONS

- Abrupt cessation may exacerbate myocardial ischemia. (5.1)
- May worsen congestive heart failure. (5.2)
- Avoid discontinuing therapy prior to major surgery. (5.3)
- Diabetes: May mask symptoms of hypoglycemia and alter glucose levels; monitor. (5.4)
- Bradycardia. (5.6)

6 ADVERSE REACTIONS

The most commonly reported adverse reactions (≥3% and greater than placebo) included the following: fatigue, dizziness, and constipation. (6.1)

To report SUSPECTED ADVERSE REACTIONS, contact ANI Pharmaceuticals, Inc. at 1-800-308-6755 or FDA at 1-800-FDA-1088 or www.fda.gov/medwatch.

7 DRUG INTERACTIONS

- CYP2D6, 1A2, or 2C19 enzyme inhibitors increase propranolol levels. (7.1)
- CYP1A2 and 2C19 inducers decrease propranolol levels. (7.1)
- Monitor prothrombin time when propranolol is co-administered with warfarin. (7.1)

8 USE IN SPECIFIC POPULATIONS

- Pregnancy: Monitor neonates whose mothers received propranolol near the time of delivery for bradycardia, hypoglycemia, and/or respiratory depression and manage accordingly. (8.1)

FULL PRESCRIBING INFORMATION

1 INDICATIONS AND USAGE

INDERAL XL is indicated for the treatment of hypertension, to lower blood pressure. Lowering blood pressure reduces the risk of fatal and nonfatal cardiovascular events, primarily strokes and myocardial infarctions. These benefits have been seen in controlled trials of antihypertensive drugs from a wide variety of pharmacologic classes, including beta-blockers.

Control of high blood pressure should be part of comprehensive cardiovascular risk management, including, as appropriate, lipid control, diabetes management, antithrombotic therapy, smoking cessation, exercise, and limited sodium intake. Many patients will require more than one drug to achieve blood pressure goals. For specific advice on goals and management, see published guidelines, such as those of the National High Blood Pressure Education Program’s Joint National Committee on Prevention, Detection, Evaluation, and Treatment of High Blood Pressure (JNC).

Numerous antihypertensive drugs, from a variety of pharmacologic classes and with different mechanisms of action, have been shown in randomized controlled trials to reduce cardiovascular morbidity and mortality, and it can be concluded that it is blood pressure reduction, and not some other pharmacologic property of the drugs, that is largely responsible for those benefits. The largest and most consistent cardiovascular outcome benefit has been a reduction in the risk of stroke, but reductions in myocardial infarction and cardiovascular mortality also have been seen regularly.

Elevated systolic or diastolic pressure causes increased cardiovascular risk, and the absolute risk increase per mm Hg is greater at higher blood pressures, so that even modest reductions of severe hypertension can provide substantial benefit. Relative risk reduction from blood pressure reduction is similar across populations with varying absolute risk, so the absolute benefit is greater in patients who are at higher risk independent of their hypertension (for example, patients with diabetes or hyperlipidemia), and such patients would be expected to benefit from more aggressive treatment to a lower blood pressure goal.

Some antihypertensive drugs have smaller blood pressure effects (as monotherapy) in black patients, and many antihypertensive drugs have additional approved indications and effects (e.g., on angina, heart failure, or diabetic kidney disease). These considerations may guide selection of therapy.

2 DOSAGE AND ADMINISTRATION

INDERAL XL should be administered once daily at bedtime and should be taken consistently either on an empty stomach or with food. Initiate dosing at 80 mg and titrate to 120 mg daily as needed for blood pressure control. Doses above 120 mg have no additional effects on blood pressure [see Clinical Studies (14.1)]. Full antihypertensive response is usually achieved within 2 to 3 weeks.

3 DOSAGE FORMS AND STRENGTHS

INDERAL XL Extended-Release Capsules are supplied as capsules containing either 80 mg (equivalent to 70.14 mg of propranolol) or 120 mg (equivalent to 105.21 mg of propranolol) of propranolol hydrochloride imprinted with “Inderal XL” using FD&C Blue #2 Aluminum Lake. In addition, the 80 mg strength is a white opaque capsule, imprinted with “80” and 1 segmented band, while the 120 mg strength is a buff opaque capsule imprinted with “120” and 3 segmented bands.

4 CONTRAINDICATIONS

INDERAL XL is contraindicated in patients with:

- Cardiogenic shock or decompensated heart failure
- Sinus bradycardia, sick sinus syndrome, and greater than first-degree block unless a permanent pacemaker is in place
- Bronchial asthma
- Known hypersensitivity (e.g., anaphylactic reaction) to propranolol hydrochloride or any of the components of INDERAL XL

5 WARNINGS AND PRECAUTIONS

5.1 Cardiac Ischemia after Abrupt Discontinuation

Following abrupt discontinuation of therapy with beta-blockers, exacerbations of angina pectoris and myocardial infarction have occurred.

When discontinuing chronically administered INDERAL XL, particularly in patients with ischemic heart disease, gradually reduce the dose over a period of 1-2 weeks and monitor the patients. If angina markedly worsens or acute coronary insufficiency develops, promptly resume therapy, at least temporarily and take other measures appropriate for the management of unstable angina. Warn patients against interruption or discontinuation of therapy without physician’s advice.

Because coronary artery disease is common and may be unrecognized, avoid abrupt discontinuation of INDERAL XL therapy even in patients treated only for hypertension.

5.2 Cardiac Failure

Beta-blockers, like INDERAL XL, can cause depression of myocardial contractility and may precipitate heart failure and cardiogenic shock. If signs or symptoms of heart failure develop, treat the patient according to recommended guidelines. It may be necessary to lower the dose of INDERAL XL or to discontinue it.

5.3 Maintain During Major Surgery

Chronically administered beta-blocking therapy, including INDERAL XL, should not be routinely withdrawn prior to major surgery; however, the impaired ability of the heart to respond to reflex adrenergic stimuli may augment the risks of general anesthesia and surgical procedures.

5.4 Hypoglycemia

Beta-blockers may prevent early warning signs of hypoglycemia, such as tachycardia, and increase the risk for severe or prolonged hypoglycemia at any time during treatment, especially in patients with diabetes mellitus or children and patients who are fasting (i.e., surgery, not eating regularly, or are vomiting). If severe hypoglycemia occurs, patients should be instructed to seek emergency treatment.

5.5 Thyrotoxicosis

INDERAL XL may mask clinical signs of hyperthyroidism, such as tachycardia. Avoid abrupt withdrawal of beta-blockade, which may precipitate a thyroid storm.

5.6 Bradycardia

Bradycardia, including sinus pause, heart block, and cardiac arrest have occurred with the use of INDERAL XL. Patients with first-degree atrioventricular block, sinus node dysfunction, or conduction disorders (including Wolff-Parkinson-White) may be at increased risk. The concomitant use of beta-adrenergic blockers and non-dihydropyridine calcium channel blockers (e.g., verapamil and diltiazem), digoxin or clonidine increases the risk of significant bradycardia. Monitor heart rate and rhythm in patients receiving INDERAL XL. If severe bradycardia develops, reduce or stop INDERAL XL.

5.7 Reduced Effectiveness of Epinephrine in Treating Anaphylaxis

Beta-adrenergic blocker-treated patients treated with epinephrine for a severe anaphylactic reaction may be less responsive to the typical doses of epinephrine. In these patients, consider other medications (e.g., intravenous fluids, glucagon).

6 ADVERSE REACTIONS

6.1 Clinical Trials Experience

Because clinical trials are conducted under widely varying conditions, adverse reaction rates observed in the clinical trials of a drug cannot be directly compared to rates in the clinical trials of another drug and may not reflect the rates observed in practice.

Adverse reactions occurring at a rate of ≥3%, excluding those reported more commonly in placebo, encountered in the INDERAL XL placebo-controlled hypertension trials and plausibly related to treatment are shown in Table 1.

Table 1. Treatment-Emergent Adverse Reactions Reported In ≥3% of Subjects

 |  | INDERAL XL
Body System | Placebo (N=88) | 80 mg (N=89) | 120mg (N=85)
Fatigue | 3 (3%) | 4 (5%) | 6 (7%)
Dizziness (except vertigo) | 2 (2%) | 6 (7%) | 3 (4%)
Constipation | 0 | 3 (3%) | 1 (1%)

6.2 Postmarketing Experience

In addition to adverse reactions reported from clinical trials, the following reactions have been identified during post-marketing use of INDERAL XL. Because these reactions are reported voluntarily from a population of uncertain size, it is not always possible to reliably estimate their frequency or establish a causal relationship to drug exposure.

The following adverse reactions were observed and have been reported with use of formulations of sustained- or immediate-release propranolol.

Allergic: Hypersensitivity reactions, including anaphylactic/anaphylactoid reactions; pharyngitis and agranulocytosis; erythematous rash, fever combined with aching and sore throat, laryngospasm, and respiratory distress.

Autoimmune: Systemic lupus erythematosus (SLE).

Cardiovascular: exacerbation of peripheral arterial disease, arterial insufficiency, usually of the Raynaud type.

Central Nervous System: Light-headedness, mental depression, insomnia, lassitude, weakness, fatigue, visual disturbances, hallucinations, vivid dreams, short-term memory loss, emotional lability, slightly clouded sensorium, paresthesia of hands.

Gastrointestinal: Nausea, vomiting, epigastric distress, abdominal cramping, diarrhea, mesenteric arterial thrombosis, ischemic colitis.

Genitourinary: Male impotence; Peyronie’s disease.

Hematologic: Agranulocytosis, nonthrombocytopenic purpura, thrombocytopenic purpura.

Musculoskeletal: Myopathy, myotonia.

Skin and mucous membranes: Stevens-Johnson syndrome, toxic epidermal necrolysis, dry eyes, exfoliative dermatitis, erythema multiforme, urticaria, alopecia, SLE-like reactions, and psoriasisiform rashes.

7 DRUG INTERACTIONS

7.1 Pharmacokinetic Drug-Drug Interactions

Impact of Propranolol on Other Drugs

Warfarin: Warfarin concentrations are increased when administered with propranolol. Monitor prothrombin time accordingly [see Clinical Pharmacology (12.7)].

Propafenone: Co-administration of propranolol increases the plasma concentrations of propafenone. Monitor patients for symptoms of excessive exposure to propafenone including bradycardia and postural hypotension [see Clinical Pharmacology (12.7)].

Impact of Other Drugs on Propranolol

CYP2D6, CYP1A2 and CYP2C19 Inhibitors: CYP2D6 inhibitors (e.g. bupropion, fluoxetine, paroxetine, quinidine), CYP1A2 inhibitors (e.g., ciprofloxacin, enoxamine, fluvoxamine) and CYP2C19 inhibitors (e.g., fluconazole, fluvoxamine, ticlopidine) increase exposure to propranolol when co-administered with INDERAL XL. Monitor patients for bradycardia and hypotension [see Clinical Pharmacology (12.7)].

CYP1A2 and CYP2C19 Inducers: CYP1A2 inducers (e.g., phenytoin, montelukast, smoking) and CYP2C19 inducers (e.g. rifampin) decrease the plasma levels of propranolol resulting in a loss of efficacy [see Clinical Pharmacology (12.7)].

Cholestyramine and Colestipol: Co-administered cholestyramine or colestipol significantly reduces the plasma concentrations of co-administered propranolol which may result in loss of efficacy [see Clinical Pharmacology (12.7)].

7.2 Pharmacodynamic Drug-Drug Interactions

Adrenergic Agonists: Beta-blockers may antagonize the antihypertensive effects of clonidine, and rebound hypertension may result if clonidine is withdrawn abruptly. If clonidine and a beta-blocker are co-administered, withdraw the beta-blocker several days before the withdrawal of clonidine.

Alpha Blockers: Co-administration of beta-blockers with alpha-blocker (e.g., prazosin) has been associated with prolongation of first dose hypotension and syncope.

Dobutamine: Propranolol may reduce sensitivity to dobutamine stress echocardiography in patients undergoing evaluation for myocardial ischemia.

Antidepressants: The hypotensive effect of MAO inhibitors or tricyclic antidepressants may be exacerbated when administered with beta-blockers. Monitor patients for postural hypotension.

Nonsteroidal Anti-Inflammatory Drugs: Nonsteroidal anti-inflammatory drugs (NSAIDs) may attenuate the antihypertensive effect of beta-adrenoreceptor blocking agents. Monitor blood pressure.

8 USE IN SPECIFIC POPULATIONS

8.1 Pregnancy

Risk Summary

Prolonged experience with propranolol in pregnant women over several decades, based on published interventional and observational studies, has not identified a drug associated risk of major birth defects, miscarriage, or other adverse maternal outcomes. Bradycardia, hypoglycemia, and respiratory depression have been observed with use of beta-blockers, including propranolol, in utero near the time of delivery. There are inconsistent reports of intrauterine growth restriction with beta-blocker use, including propranolol, during pregnancy. Untreated hypertension during pregnancy can lead to serious adverse outcomes for the mother and the fetus (see Clinical Considerations and Data).

The estimated background risk of major birth defects and miscarriage for the indicated population is unknown. All pregnancies have a background risk of birth defect, loss, or other adverse outcomes. In the U.S. general population, the estimated background risk of major birth defects and miscarriage in clinically recognized pregnancies is 2% to 4% and 15% to 20%, respectively.

Clinical Considerations

Disease-Associated Maternal and/or Embryo/Fetal Risk

Hypertension in pregnancy increases the maternal risk for pre-eclampsia, gestational diabetes, premature delivery, and delivery complications (e.g., need for cesarean section, and post-partum hemorrhage) Hypertension increases the fetal risk for intrauterine growth restriction and intrauterine death. Pregnant women with hypertension should be carefully monitored and managed accordingly.

Fetal/Neonatal Adverse Reactions

Propranolol crosses the placenta. Neonates born to mothers who are receiving propranolol during pregnancy, may be at risk for bradycardia, hypoglycemia, and respiratory depression. Monitor neonates exposed to propranolol during pregnancy and manage accordingly.

Data

Animal Data

In a series of reproductive and developmental toxicology studies, propranolol was given to rats by gavage or in the diet throughout pregnancy and lactation. At doses of 150 mg/kg/day, but not at doses of 80 mg/kg/day (equivalent to the maximum recommended human oral daily dose (MRHD) on a body surface area basis), treatment was associated with embryotoxicity (reduced litter size and increased resorption rates) as well as neonatal toxicity (deaths). Propranolol HCl was also administered (in the feed) to rabbits (throughout pregnancy and lactation) at doses as high as 150 mg/kg/day (about 5 times the MRHD). No evidence of embryo or neonatal toxicity was noted.

8.2 Lactation

Risk Summary

Propranolol is present in human milk at low levels, but the related risk to a breastfed infant is unknown. There are no data on the effects of propranolol on milk production.

The developmental and health benefits of breastfeeding should be considered along with the mother’s clinical need for INDERAL XL and any potential adverse effects on the breastfed child from INDERAL XL or from the underlying maternal condition.

8.3 Females and Males of Reproductive Potential

Infertility

Males

Based on the published literature, beta-blockers, including propranolol, may cause erectile dysfunction. In rats, propranolol inhibits spermatogenesis [see Nonclinical Toxicology (13.1)].

8.4 Pediatric Use

Safety and effectiveness of propranolol in pediatric patients have not been established.

8.5 Geriatric Use

Clinical studies of INDERAL XL did not include sufficient numbers of subjects aged 65 and over to determine whether they respond differently from younger subjects. Other reported clinical experience has not identified differences in responses between the elderly and younger patients. In general, dose selection for an elderly patient should be cautious, usually starting at the low end of the dosing range, reflecting the greater frequency of decreased hepatic, renal, or cardiac function, and of concomitant disease or other drug therapy.

8.6 Renal Impairment

The exposure to propranolol is increased in patients with renal impairment. Initiate INDERAL XL therapy in patients with impaired renal function at the lowest dose (80 mg) once daily and monitor patients for marked bradycardia and hypotension [see Clinical Pharmacology (12.6)].

8.7 Hepatic Impairment

The exposure to propranolol is increased in patients with hepatic impairment. Initiate INDERAL XL therapy in patients with impaired hepatic function at the lowest dose (80 mg) once daily and monitor patients for marked bradycardia and hypotension [see Clinical Pharmacology (12.6)].

10 OVERDOSAGE

Most overdoses of propranolol are mild and respond to supportive care.

Propranolol is not significantly dialyzable.

Hypotension and bradycardia have been reported following propranolol overdose and should be treated appropriately. Glucagon can exert potent inotropic and chronotropic effects and may be particularly useful for the treatment of hypotension or depressed myocardial function after a propranolol overdose.

Glucagon should be administered as 50 to 150 mcg/kg intravenously followed by continuous drip of 1 to 5 mg/hour for positive chronotropic effect. Isoproterenol, dopamine or phosphodiesterase inhibitors may also be useful. Epinephrine, however, may provoke uncontrolled hypertension. Bradycardia can be treated with atropine or isoproterenol. Serious bradycardia may require temporary cardiac pacing.

Monitor the electrocardiogram, pulse, blood pressure, neurobehavioral status and intake and output balance. Isoproterenol and aminophylline may be used for bronchospasm.

11 DESCRIPTION

INDERAL XL contains propranolol hydrochloride, a nonselective, beta-adrenergic receptor-blocking agent for oral administration, as an extended-release product. INDERAL XL capsules contain sustained-release beads. Each of the beads contains propranolol hydrochloride and is coated with dual membranes. These membranes are designed to retard release of propranolol hydrochloride for several hours after ingestion followed by the sustained release of propranolol.

INDERAL XL is available as 80 mg and 120 mg capsules for oral administration.

- Each 80 mg capsule contains 80 mg propranolol hydrochloride USP (equivalent to 70.14 mg of propranolol).
- Each 120 mg capsule contains 120 mg propranolol hydrochloride USP (equivalent to 105.21 mg of propranolol).

The active ingredient in INDERAL XL is a synthetic beta-adrenergic receptor-blocking agent chemically described as 1-(Isopropylamino)-3-(1-naphthyloxy)-2-propanol hydrochloride. Its structural formula is:

Propranolol hydrochloride is a stable, white, crystalline solid, which is readily soluble in water and ethanol. Its molecular weight is 295.81. Each capsule for oral administration contains sugar spheres, ethylcellulose, povidone, hypromellose phthalate, diethyl phthalate, hypromellose, polyethylene glycol, gelatin, titanium dioxide. The ink contains FD&C Blue #2 Aluminum Lake. In addition, INDERAL XL 120 mg capsules contain yellow iron oxide.

12 CLINICAL PHARMACOLOGY

12.1 Mechanism of Action

The mechanism of the antihypertensive effect of propranolol has not been established. Among factors that contribute to the antihypertensive action are: (1) decreased cardiac output, (2) inhibition of renin release by the kidneys, and (3) diminution of tonic sympathetic nerve outflow from vasomotor centers in the brain. Although total peripheral resistance may increase initially, it readjusts to or below the pretreatment level with chronic use. Effects of propranolol on plasma volume appear to be minor and somewhat variable.

12.2 Pharmacodynamics

Propranolol is a nonselective, beta-adrenergic receptor-blocking agent possessing no other autonomic nervous system activity. It specifically competes with beta-adrenergic receptor-stimulating agents for available receptor sites. Of the 2 enantiomers of propranolol, the S-enantiomer blocks beta-adrenergic receptors. When access to beta-receptor sites is blocked by propranolol, chronotropic, inotropic, and vasodilator responses to beta-adrenergic stimulation are decreased proportionately. At dosages greater than required for beta-blockade, propranolol also exerts a quinidine-like or anesthetic-like membrane action, which affects the cardiac action potential. The significance of the membrane action in the treatment of arrhythmias is uncertain.

12.3 Pharmacokinetics

Absorption: Propranolol is highly lipophilic and is almost completely absorbed after oral administration. However, it undergoes high first-pass metabolism by the liver, and, on average, only about 25% of propranolol reaches the systemic circulation.

A single-dose, food-effect study in 36 healthy subjects showed that a high fat meal administered with INDERAL XL at 10 p.m., increased the lag time from 3 to 5 hours and the time to reach the maximum concentration from 11.5 to 15.4 hours, with no effect on the AUC.

Following multiple-dose administration of INDERAL XL at 10 p.m. under fasting conditions, the steady state lag time was between 4 and 5 hours and propranolol peak plasma concentrations were reached approximately 12 to 14 hours after dosing. Propranolol trough levels were achieved 24 to 27 hours after dosing, and persisted for 3 to 5 hours after the next dose.

The plasma levels of propranolol showed dose-proportional increases after single and multiple administration of 80, 120, and 160 mg of INDERAL XL.

At steady state, the bioavailability of a 160 mg dose of INDERAL XL and propranolol hydrochloride long-acting capsules did not differ significantly.

Distribution: Approximately 90% of circulating propranolol is bound to plasma proteins (albumin and alpha1 acid glycoprotein). The binding is enantiomer-selective. The S-isomer is preferentially bound to alpha1 glycoprotein and the R-isomer preferentially bound to albumin. The volume of distribution of propranolol is approximately 4 liters.

Metabolism and Elimination: Propranolol is extensively metabolized with most metabolites appearing in the urine. Propranolol is metabolized through 3 primary routes: Aromatic hydroxylation (mainly 4-hydroxylation), N-dealkylation followed by further side-chain oxidation, and direct glucuronidation. It has been estimated that the percentage contributions of these routes to total metabolism are 42%, 41%, and 17%, respectively, but with considerable variability between individuals. The 4 major metabolites are propranolol glucuronide, naphthyloxylactic acid, and glucuronic acid and sulfate conjugates of 4-hydroxy propranolol.

In vitro studies have indicated that the aromatic hydroxylation of propranolol is catalyzed mainly by polymorphic CYP2D6. Side-chain oxidation is mediated mainly by CYP1A2 and to some extent by CYP2D6. 4-hydroxy propranolol is a weak inhibitor of CYP2D6.

Propranolol is also a substrate for CYP2C19 and a substrate for the intestinal efflux transporter, p-glycoprotein (p-gp). Studies suggest however that p-gp is not dose-limiting for intestinal absorption of propranolol in the usual therapeutic dose range.

In healthy subjects, no difference was observed between CYP2D6 extensive metabolizers (EMs) and poor metabolizers (PMs) with respect to oral clearance or elimination half-life. Partial clearance to 4-hydroxy propranolol was significantly higher and to naphthyloxylactic acid was significantly lower in EMs than PMs.

In normal subjects receiving oral doses of racemic propranolol, S-enantiomer concentrations exceeded those of the R-enantiomer by 40 to 90% as a result of stereoselective hepatic metabolism.

The elimination half-life of propranolol was approximately 8 hours.

12.6 Specific Populations

Pediatric: The pharmacokinetics of INDERAL XL have not been investigated in patients younger than 18 years of age.

Geriatric: The pharmacokinetics of INDERAL XL have not been investigated in patients older than 65 years. In a study of 12 elderly (62 to 79 years old) and 12 young (25 to 33 years old) healthy subjects administered immediate-release propranolol, the clearance of the S-enantiomer of propranolol was decreased in the elderly. Additionally, the half-lives of both R- and S-propranolol were prolonged in the elderly compared with the young (11 hours versus 5 hours).

Gender: In a dose-proportionality study, the pharmacokinetics of INDERAL XL were evaluated in 22 male and 14 female healthy volunteers. Following single doses under fasting conditions, the mean AUC and Cmax were about 49% and 16% higher for females across the dosage range. The mean elimination half-life was longer in females than in males (11 hours versus 7.5 hours).

Race: A study conducted in 12 white and 13 African-American male subjects taking immediate-release propranolol showed, at steady state, the clearance of R- and S-propranolol were about 76% and 53% higher in African-Americans than in whites, respectively.

Renal Impairment: The pharmacokinetics of propranolol after administration of INDERAL XL have not been evaluated in patients with renal impairment. In a study conducted in 5 patients with chronic renal failure, 6 patients on regular dialysis, and 5 healthy subjects, who received a single oral dose of 40 mg of propranolol, the peak plasma concentrations (Cmax) of propranolol in the chronic renal failure group were 3- to 5-fold (161±41 ng/mL) those observed in the dialysis patients (47±9 ng/mL) and in the healthy subjects (26±1 ng/mL). Propranolol plasma clearance was also reduced in the patients with chronic renal failure.

Chronic renal failure has been associated with a decrease in drug metabolism via down regulation of hepatic cytochrome P450 activity.

Propranolol is not significantly dialyzable.

Hepatic Impairment: The pharmacokinetics of propranolol after administration of INDERAL XL have not been evaluated in patients with hepatic impairment. However, propranolol is extensively metabolized by the liver. In a study conducted in 7 patients with cirrhosis and 9 healthy subjects receiving 80 mg oral propranolol every 8 hours for 7 doses, the steady-state unbound propranolol concentration in patients with cirrhosis was 3-fold that of controls. In cirrhosis, the half-life increased to 11 hours compared to 4 hours.

12.7 Drug-Drug Interactions

Impact of Propranolol on Other Drugs

The effect of propranolol on exposure to other drugs is shown in Table 2.

Table 2 Impact of propranolol on other drugs

Other drug | Effect on their exposure
Amide anesthetics (lidocaine, bupivacaine, mepivicaine) | Increased
Warfarin | Increased
Propafenone | Increased >200%
Nifedipine | Increased 80%
Verapamil | None
Pravastatin, lovastatin | Decreased 20%
Fluvastatin | None
Zolmitriptan | Increased 60%
Rizatriptan | Increased 80%
Thioridazine | Increased 370%
Diazepam | Increased
Oxazepam, triazolam, lorazepam, alprazolam | None
Theophylline | Increased 70%

Impact of Other Drugs on Propranolol

The effect of propranolol on exposure to other drugs is shown in Table 3.

Table 3 Impact of other drugs on exposure to propranolol

Other drug | Effect on propranolol exposure
Inhibitors of CYP2D6, CYP1A2, or CYP2C19 | Increased
Inducers of CYP1A2 or CYP2C19 | Decreased
Quinidine | Increased >200%
Nisoldipine | Increased 50%
Nicardipine | Increased 80%
Chlorpromazine | Increased 70%
Cimetidine | Increased 50%
Cholestyramine, colestipol | Decreased 50%
Alcohol | Increased
Diazepam | None
Verapamil | None
Metoclopramide | None
Ranitidine | None
Lansoprazole | None
Omeprazole | None
Alcohol | Increase acutely or decrease chronically
Propafenone | Increased 200%
Quinidine | Increased 200%
Cimetidine | Increased 40%
Aluminum hydroxide | Decreased 50%
Diazepam | None
Nisoldipine, nicardipine, nifedipine | Increased 50-80%

13 NONCLINICAL TOXICOLOGY

13.1 Carcinogenesis, Mutagenesis, Impairment of Fertility

Carcinogenesis

In dietary administration studies in which mice and rats were treated with propranolol HCl for up to 18 months at doses of up to 150 mg/kg/day, there was no evidence of drug-related tumorigenesis. On a body surface area basis, this dose in the mouse and rat is, respectively, about equal to and about twice the MRHD of 640 mg propranolol HCl.

Mutagenesis

Based on differing results from Ames tests performed by different laboratories, a genotoxic effect of propranolol HCl is equivocal in bacteria (S. typhimurium strain TA 1538).

Impairment of Fertility

Propranolol effects on fertility are also equivocal. No effects on fertility were reported in a study with both male and female rats exposed to propranolol HCl in their diets at concentrations of up to 0.05% (about 50 mg/kg body weight and less than the MRHD), from 60 days prior to mating and throughout pregnancy and lactation for 2 generations. Another study in rats receiving oral propranolol (7.5 and 15 mg/kg for 60 days) reported decreased sperm motility, increased sperm abnormalities and decreased testosterone; all effects were fully reversible within 60 days of propranolol discontinuation. A separate study in male mice receiving oral propranolol (10 or 15 mg/kg body weight) in water once daily reported both doses impaired spermatogenesis and reduced sperm motility; fewer females became pregnant and pregnant females had fewer implantation sites and viable fetuses. In addition, when female rabbits were injected with 7 mg/kg propranolol at three-hour intervals (8 times daily is about twice the MHRD), sperm counts in the oviducts were reduced and fewer sperm attached to and penetrated the eggs.

14 CLINICAL STUDIES

14.1 Hypertension

In a double-blind, parallel dose-response study in patients with mild-to-moderate hypertension (n=434), doses of INDERAL XL from 80 to 640 mg were taken once daily at approximately 10 p.m. INDERAL XL significantly lowered sitting systolic and diastolic blood pressure when measurements were taken approximately 16 hours later. The placebo-subtracted diastolic blood pressure effect for the 80- and 120-mg doses was -3.0 and -4.0 mm Hg, respectively. Higher doses of INDERAL XL (160, 640 mg) had no additional blood-pressure lowering effect when compared with 120 mg. The antihypertensive effects of INDERAL XL were seen in the elderly (≥65 years old) and men and women. There were too few non-white patients to assess the efficacy of INDERAL XL in these patients.

16 HOW SUPPLIED/STORAGE AND HANDLING

INDERAL XL (propranolol hydrochloride) Extended-Release Capsules are available as follows:

Each white opaque capsule, imprinted with ‘Inderal XL’, ‘80’, and 1 segmented band, contains 80 mg of propranolol hydrochloride USP (equivalent to 70.14 mg of propranolol) and are available as follows:
Bottles of 30 NDC 62559-600-30
Bottles of 7 NDC 62559-600-77 (professional sample)
Bottles of 14 NDC 62559-600-14 (professional sample).

Each buff opaque capsule, imprinted with ‘Inderal XL’, ‘120’, and 3 segmented bands, contains 120 mg of propranolol hydrochloride USP (equivalent to 105.21 mg of propranolol) and are available as follows:
Bottles of 30 NDC 62559-601-30
Bottles of 7 NDC 62559-601-77 (professional sample)
Bottles of 14 NDC 62559-601-14 (professional sample).

Storage: Store at 25ºC (77ºF); excursions permitted to 15º and 30ºC (59º and 86ºF) [see USP Controlled Room Temperature] in a tightly closed container.

17 PATIENT COUNSELING INFORMATION

- Advise patients not to interrupt or discontinue using INDERAL XL without a physician’s advice.
- Advise patients with heart failure to consult their physician if they experience signs or symptoms of worsening heart failure such as weight gain or increasing shortness of breath.
- Inform patients or caregivers that there is a risk of hypoglycemia when INDERAL XL is given to patients who are fasting or who are vomiting. Instruct patients or caregivers how to monitor for signs of hypoglycemia [see Warnings and Precautions (5.4)].

For further product information, please visit www.anipharmaceuticals.com or call 1-800-308-6755.

Distributed by:
ANI Pharmaceuticals, Inc.
Baudette, MN 56623

INDERAL XL®, a DIFFUCAPS® drug delivery product manufactured by Adare Pharmaceuticals, Inc., Vandalia, OH 45377

10050 Rev 06/23

PACKAGE/LABEL PRINCIPAL DISPLAY PANEL

INDERAL® XL (propranolol hydrochloride) Extended Release Capsules, 80 mg
NDC 62559-600-30
Rx only
30 Capsules

Package/Label Display Panel

INDERAL® XL (propranolol hydrochloride) Extended Release Capsules, 120 mg
NDC 62559-601-30
Rx only
30 Capsules